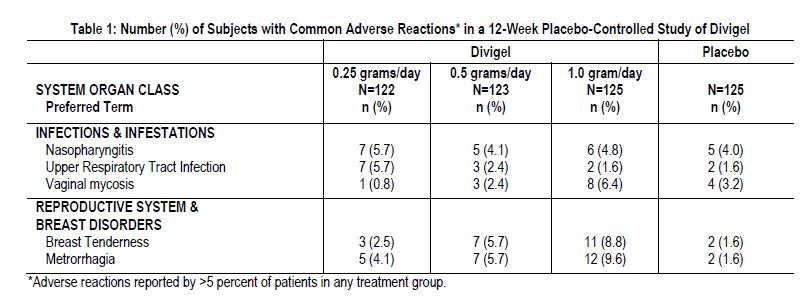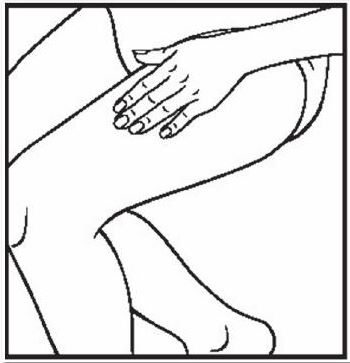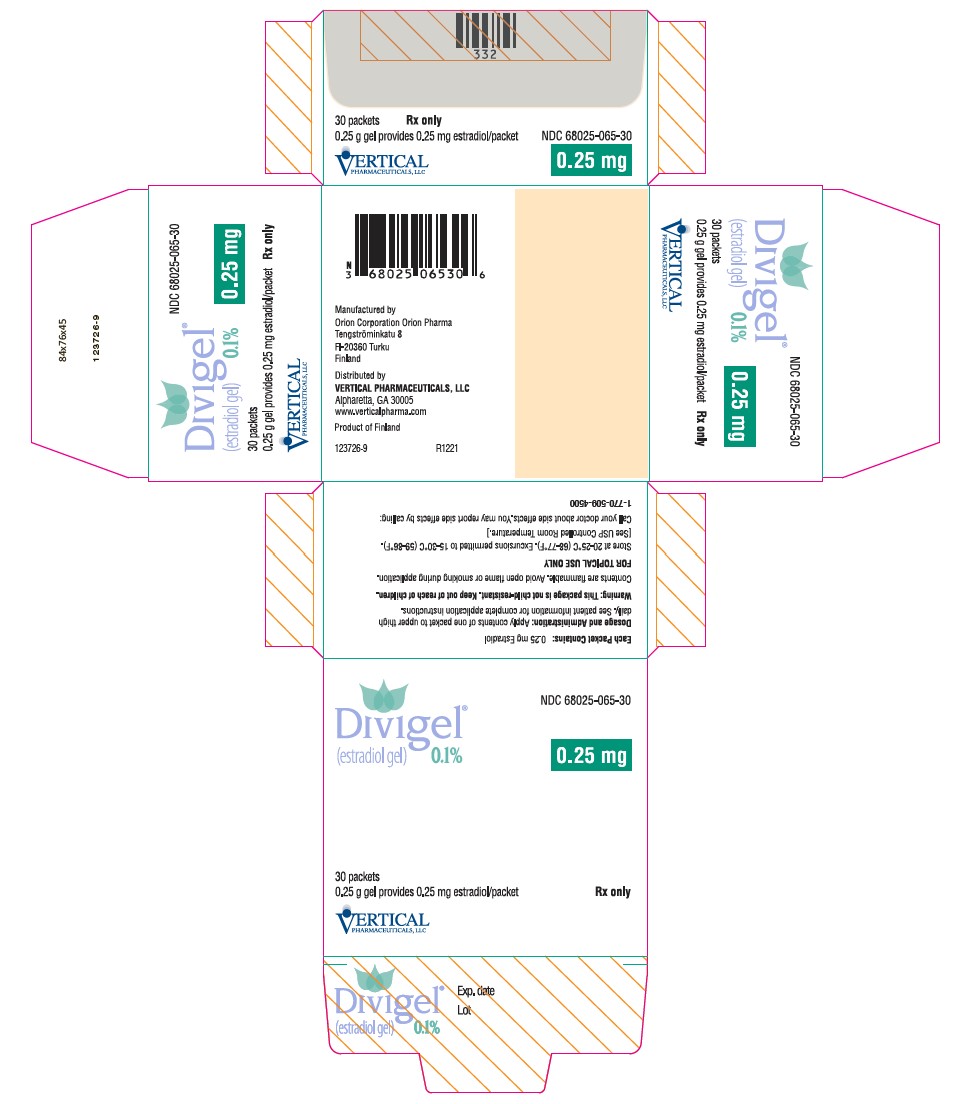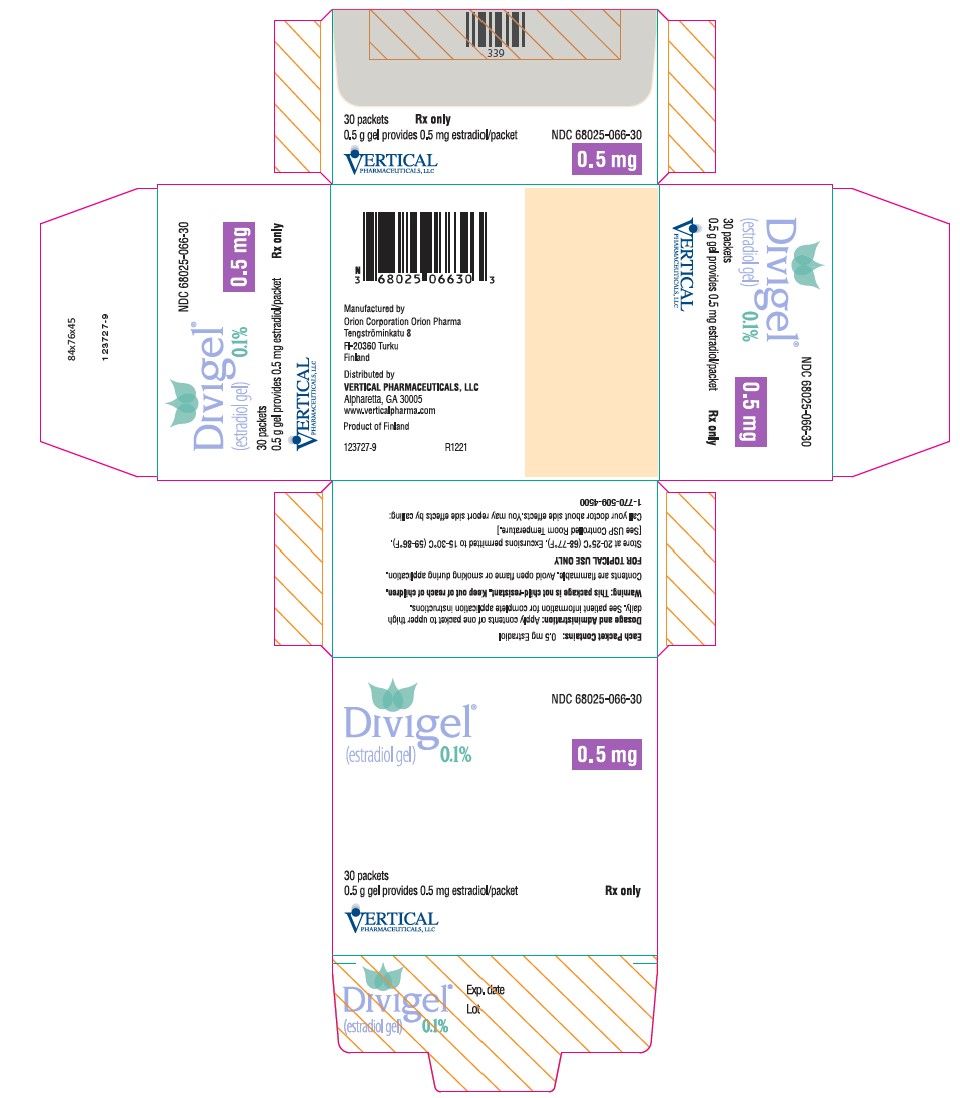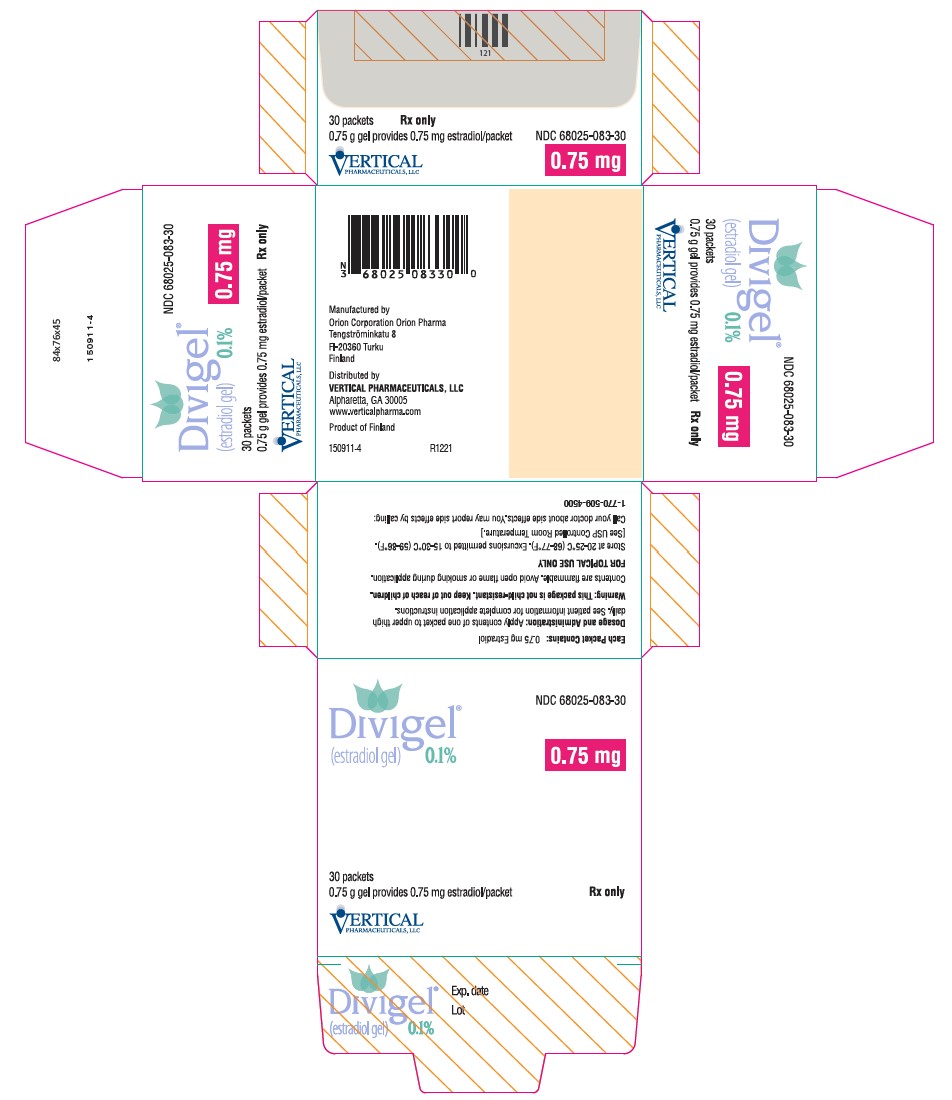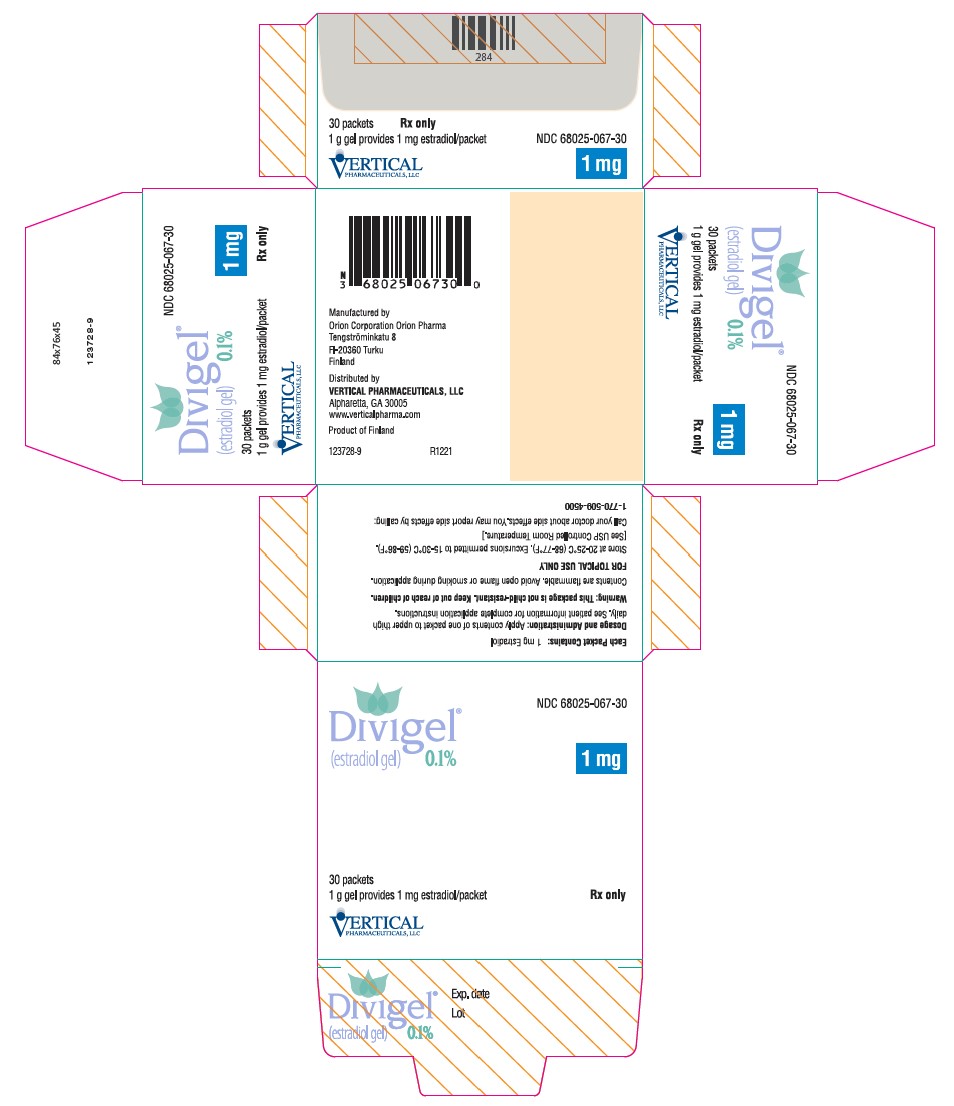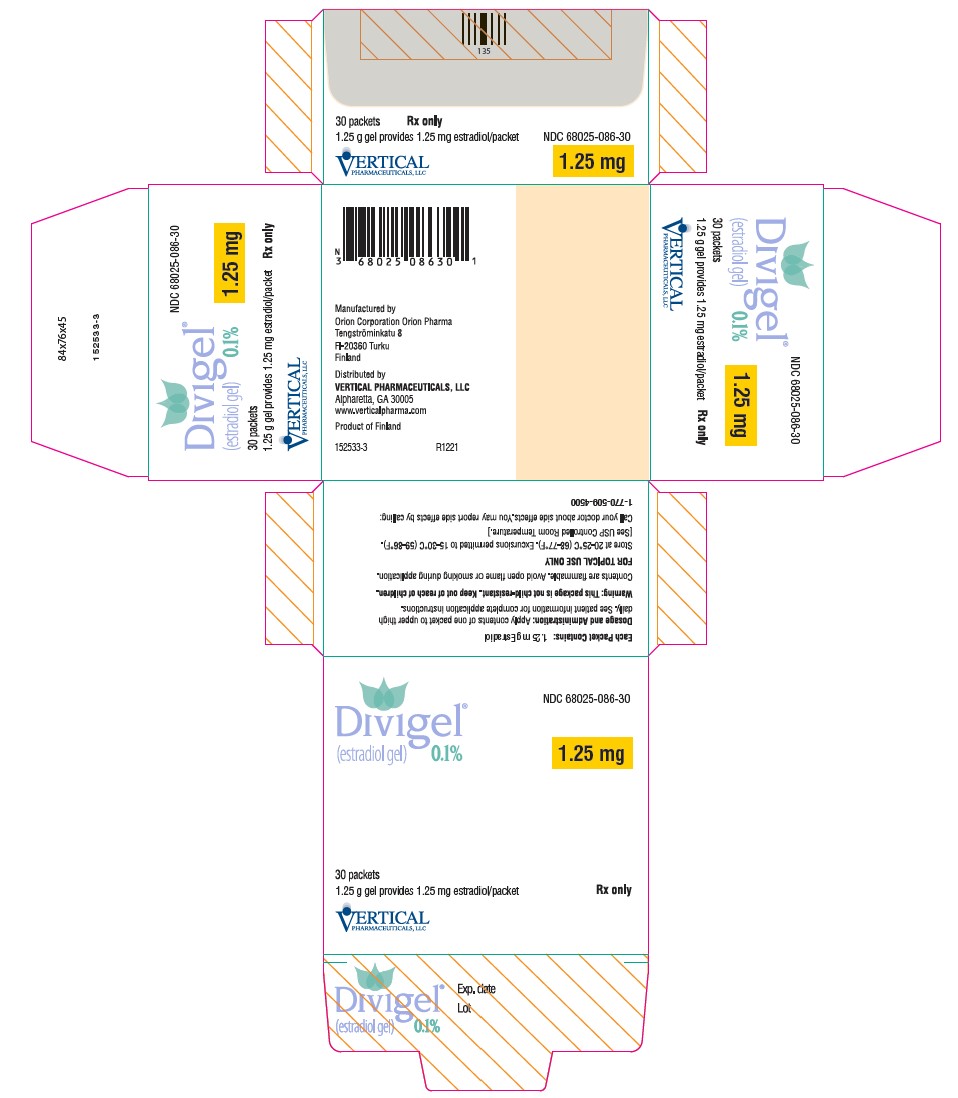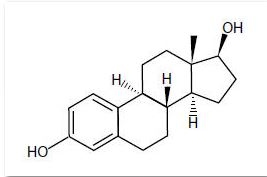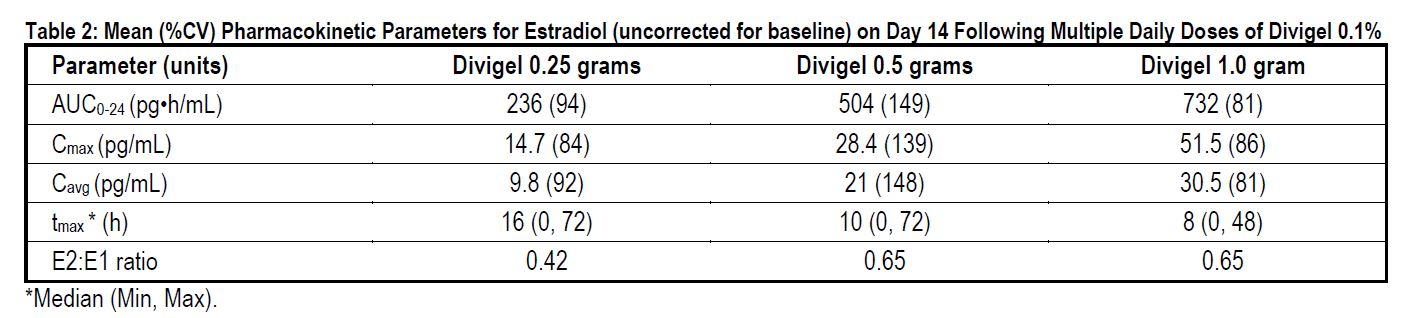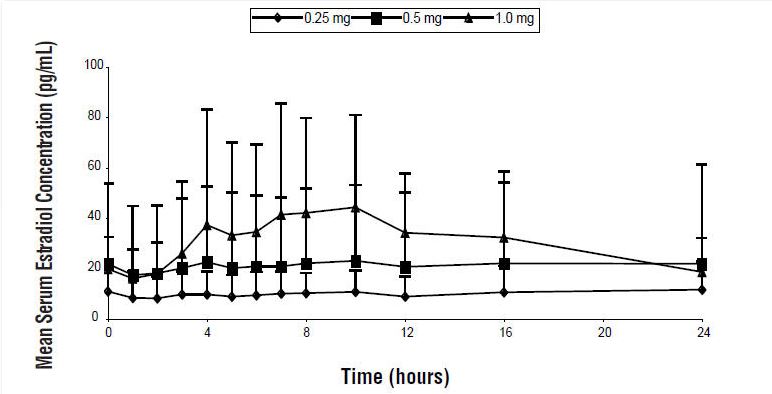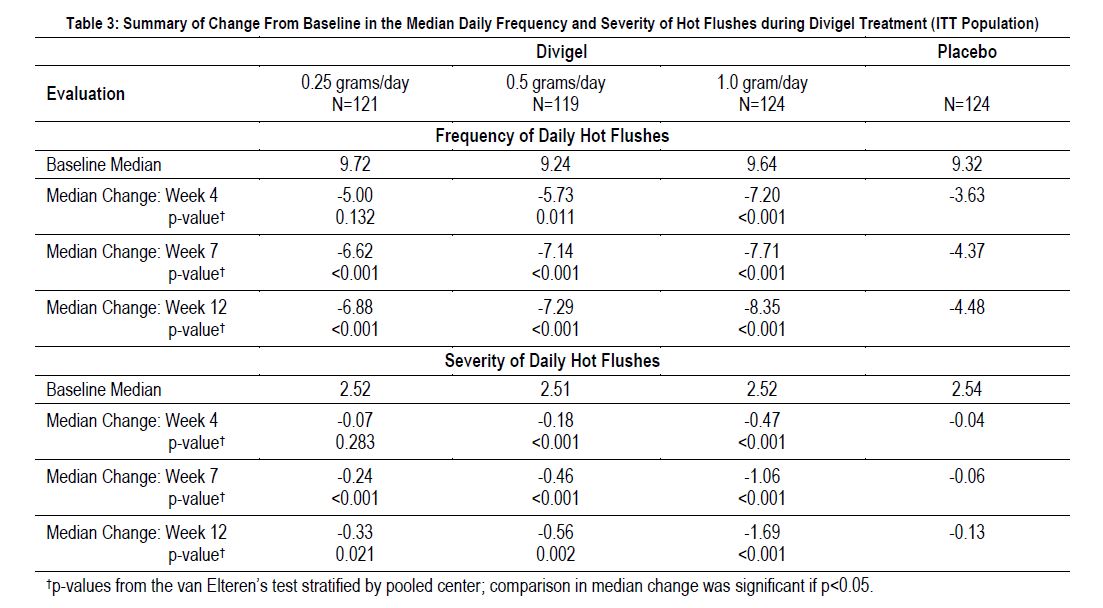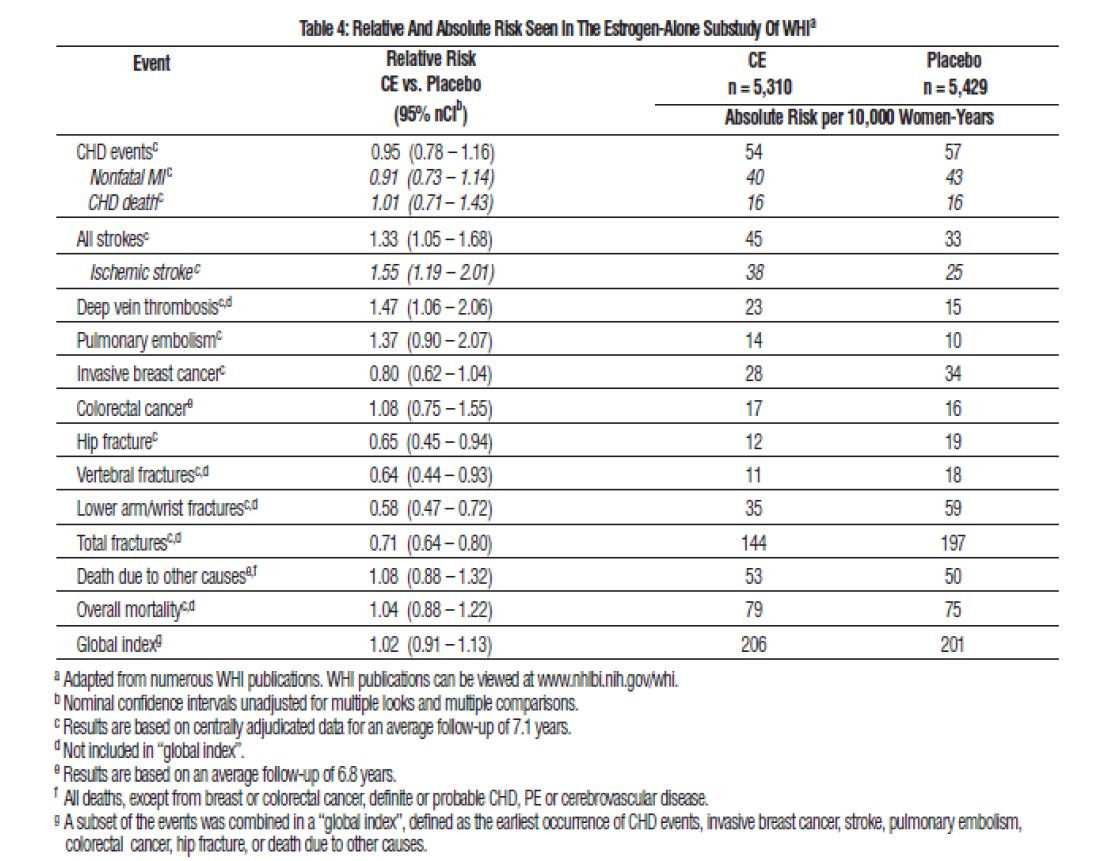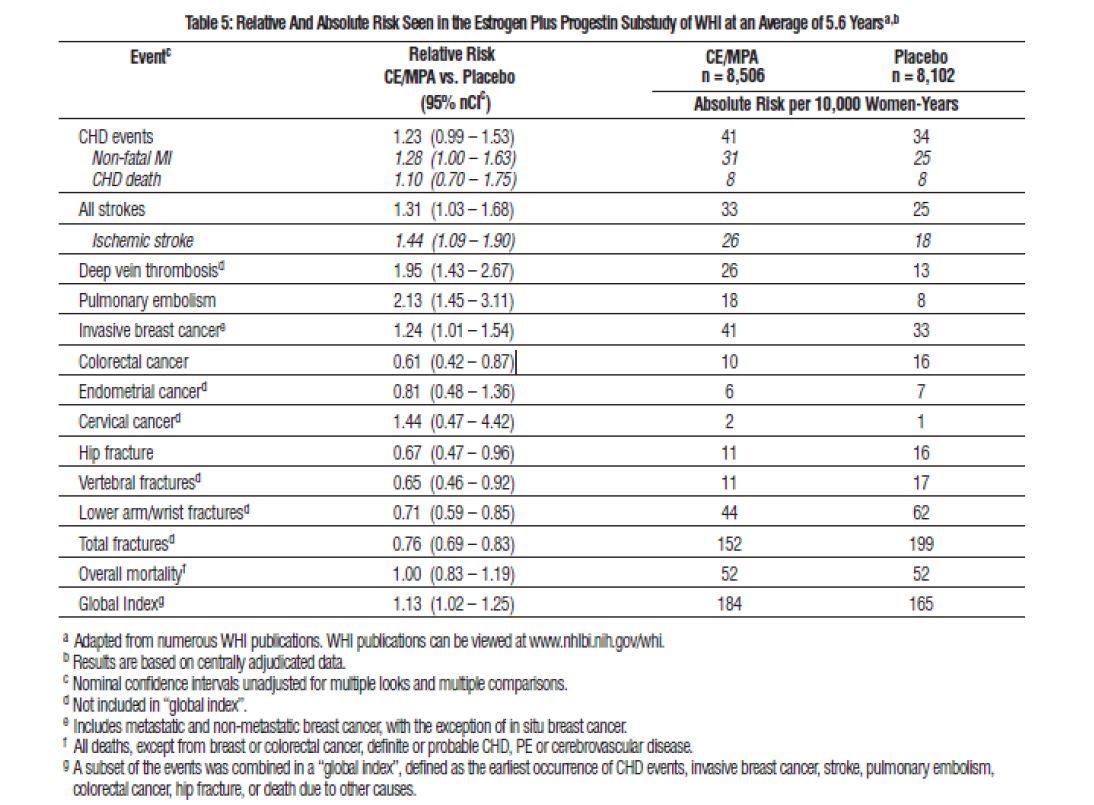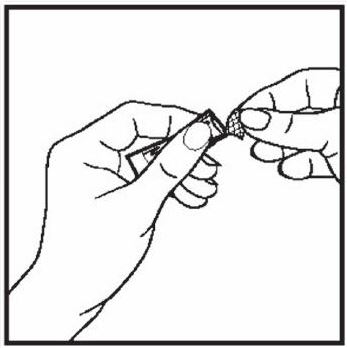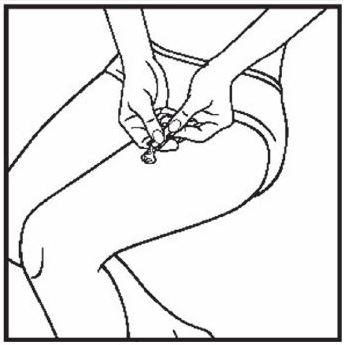 DRUG LABEL: DIVIGEL
NDC: 68025-067 | Form: GEL
Manufacturer: Vertical Pharmaceuticals, LLC
Category: prescription | Type: HUMAN PRESCRIPTION DRUG LABEL
Date: 20231121

ACTIVE INGREDIENTS: ESTRADIOL 1 mg/1 g
INACTIVE INGREDIENTS: CARBOMER HOMOPOLYMER TYPE B (ALLYL PENTAERYTHRITOL CROSSLINKED); CARBOMER HOMOPOLYMER TYPE C; ALCOHOL; PROPYLENE GLYCOL; WATER; TROLAMINE

HIGHLIGHTS OF PRESCRIBING INFORMATION

These highlights do not include all the information needed to use DIVIGEL safely and effectively. See full prescribing information for DIVIGEL.
DIVIGEL® (estradiol gel), for topical use
Initial U.S. Approval: 1975

WARNING: ENDOMETRIAL CANCER, CARDIOVASCULAR DISORDERS, PROBABLE DEMENTIA and BREAST CANCER

See full prescribing information for complete boxed warning.

Estrogen-Alone Therapy

- There is an increased risk of endometrial cancer in a woman with a uterus who uses unopposed estrogens (5.2)
- The Women’s Health Initiative (WHI) estrogen-alone substudy reported increased risks of stroke and deep vein thrombosis (DVT) (5.1)
- The WHI Memory Study (WHIMS) estrogen-alone ancillary study of WHI reported an increased risk of probable dementia in postmenopausal women 65 years of age and older (5.3)
- Do not use estrogen-alone therapy for the prevention of cardiovascular disease or dementia (5.1, 5.3)

Estrogen Plus Progestin Therapy

- The WHI estrogen plus progestin substudy reported increased risks of pulmonary embolism (PE), DVT, stroke, and myocardial infarction (MI) (5.1)
- The WHI estrogen plus progestin study reported increased risks of invasive breast cancer (5.2)
- The WHIMS estrogen plus progestin ancillary study of WHI reported an increased risk of probable dementia in postmenopausal women 65 years of age and older (5.3)
- Do not use estrogen plus progestogen therapy for the prevention of cardiovascular disease or dementia (5.1, 5.3)

RECENT MAJOR CHANGES

Warnings and Precautions, Malignant Neoplasms (5.2) 11/2023

1 INDICATIONS AND USAGE

Divigel is an estrogen indicated for the treatment of moderate to severe vasomotor symptoms due to menopause (1.1).

2 DOSAGE AND ADMINISTRATION

Daily administration of 0.25 to 1.25 grams of Divigel to the right or left upper thigh on alternating days. Women should be started with the lowest effective dose and the dose should be evaluated periodically (2).

3 DOSAGE FORMS AND STRENGTHS

Gel: 0.25, 0.5, 0.75, 1.0, and 1.25 gram-filled single-dose foil packets containing 0.25, 0.5, 0.75, 1.0, and 1.25 mg estradiol, respectively (3)

4 CONTRAINDICATIONS

- Undiagnosed abnormal genital bleeding (4)
- Breast cancer or a history of breast cancer (4, 5.2)
- Estrogen-dependent neoplasia (4, 5.2)
- Active DVT, PE, or history of these conditions (4, 5.1)
- Active arterial thromboembolic disease (e.g., stroke and MI), or history of these conditions (4, 5.1)
- Known anaphylactic reaction, angioedema, or hypersensitivity to Divigel (4)
- Hepatic impairment or disease (4, 5.10)
- Protein C, protein S, or antithrombin deficiency, or other known thrombophilic disorders (4)

5 WARNINGS AND PRECAUTIONS

- Estrogens increase the risk of gallbladder disease (5.4)
- Discontinue estrogen if severe hypercalcemia, loss of vision, severe hypertriglyceridemia or cholestatic jaundice occurs (5.5, 5.6, 5.9, 5.10)
- Monitor thyroid function in women on thyroid replacement therapy (5.11, 5.22)

6 ADVERSE REACTIONS

The most common adverse reactions (incidence >5 percent and greater than placebo) in any Divigel treatment group are metrorrhagia, breast tenderness, vaginal mycosis, nasopharyngitis, and upper respiratory tract infection (6.1).

To report SUSPECTED ADVERSE REACTIONS, contact VERTICAL PHARMACEUTICALS, LLC at 1-800-444-5164 or FDA at 1-800-FDA-1088 or www.fda.gov/medwatch.

7 DRUG INTERACTIONS

- Inducers and inhibitors of CYP3A4 may affect estrogen drug metabolism and decrease or increase the estrogen plasma concentration (7).

FULL PRESCRIBING INFORMATION

WARNING: ENDOMETRIAL CANCER, CARDIOVASCULAR DISORDERS, PROBABLE DEMENTIA and BREAST CANCER

Estrogen-Alone Therapy

Endometrial Cancer

There is an increased risk of endometrial cancer in a woman with a uterus who uses unopposed estrogens. Adding a progestogen to estrogen therapy has been shown to reduce the risk of endometrial hyperplasia, which may be a precursor to endometrial cancer. Perform adequate diagnostic measures, including directed or random endometrial sampling when indicated, to rule out malignancy in postmenopausal women with undiagnosed persistent or recurring abnormal genital bleeding [see Warnings and Precautions (5.2)].

Cardiovascular Disorders and Probable Dementia

The Women's Health Initiative (WHI) estrogen-alone substudy reported increased risks of stroke and deep vein thrombosis (DVT) in postmenopausal women (50 to 79 years of age) during 7.1 years of treatment with daily oral conjugated estrogens (CE) [0.625 mg]-alone, relative to placebo [see Warnings and Precautions (5.1), and Clinical Studies (14.2)].

The WHI Memory Study (WHIMS) estrogen-alone ancillary study of WHI reported an increased risk of developing probable dementia in postmenopausal women 65 years of age and older during 5.2 years of treatment with daily CE (0.625 mg)-alone, relative to placebo. It is unknown whether this finding applies to younger postmenopausal women [see Warnings and Precautions (5.3), Use in Specific Populations (8.5), and Clinical Studies (14.3)].

Do not use estrogen-alone therapy for the prevention of cardiovascular disease or dementia [see Warnings and Precautions (5.1, 5.3), and Clinical Studies (14.2, 14.3)].

Only daily oral 0.625 mg CE was studied in the estrogen-alone substudy of the WHI. Therefore, the relevance of the WHI findings regarding adverse cardiovascular events and dementia to lower CE doses, other routes of administration, or other estrogen-alone products is not known. Without such data, it is not possible to definitively exclude these risks or determine the extent of these risks for other products. Discuss with your patient the benefits and risks of estrogen-alone therapy, taking into account her individual risk profile.

Prescribe estrogens with or without progestogens at the lowest effective doses and for the shortest duration consistent with treatment goals and risks for the individual woman.

Estrogen Plus Progestin Therapy

Cardiovascular Disorders and Probable Dementia

The WHI estrogen plus progestin substudy reported increased risks of pulmonary embolism (PE), DVT, stroke, and myocardial infarction (MI) in postmenopausal women (50 to 79 years of age) during 5.6 years of treatment with daily oral CE (0.625 mg) combined with medroxyprogesterone acetate (MPA) [2.5 mg], relative to placebo [see Warnings and Precautions (5.1), and Clinical Studies (14.2)].

The WHIMS estrogen plus progestin ancillary study of the WHI reported an increased risk of developing probable dementia in postmenopausal women 65 years of age and older during 4 years of treatment with daily CE (0.625 mg) combined with MPA (2.5 mg), relative to placebo. It is unknown whether this finding applies to younger postmenopausal women [see Warnings and Precautions (5.3), Use in Specific Populations (8.5), and Clinical Studies (14.3)].

Do not use estrogen plus progestogen therapy for the prevention of cardiovascular disease or dementia [see Warnings and Precautions (5.1, 5.3), and Clinical Studies (14.2, 14.3)].

Breast Cancer

The WHI estrogen plus progestin substudy demonstrated an increased risk of invasive breast cancer [see Warnings and Precautions (5.2), and Clinical Studies (14.2)].

Only daily oral 0.625 mg CE and 2.5 mg MPA were studied in the estrogen plus progestin substudy of the WHI. Therefore, the relevance of the WHI findings regarding adverse cardiovascular events, dementia, and breast cancer to lower CE plus other MPA doses, other routes of administration, or other estrogen plus progestogen products is not known. Without such data, it is not possible to definitively exclude these risks or determine the extent of these risks for other products. Discuss with your patient the benefits and risks of estrogen plus progestogen therapy, taking into account her individual risk profile.

Prescribe estrogens with or without progestogens at the lowest effective doses and for the shortest duration consistent with treatment goals and risks for the individual woman.

RECENT MAJOR CHANGES

Warnings and Precautions, Malignant Neoplasms (5.2)11/2023

2 DOSAGE AND ADMINISTRATION

Generally, when estrogen is prescribed for a postmenopausal woman with a uterus, consider addition of a progestogen to reduce the risk of endometrial cancer.

Generally, a woman without a uterus, does not need a progestogen in addition to her estrogen therapy. In some cases, however, hysterectomized women who have a history of endometriosis may need a progestogen [see Warnings and Precautions (5.2, 5.14)].

Use estrogen-alone, or in combination with a progestogen, at the lowest effective dose and for the shortest duration consistent with treatment goals and risks for the individual woman. Reevaluate postmenopausal women periodically as clinically appropriate to determine whether treatment is still necessary.

2.1 Treatment of Moderate to Severe Vasomotor Symptoms due to Menopause

Start therapy with the 0.25 grams applied once daily on the skin of either the right or left upper thigh. Adjust the dose up to a maximum of 1.25 grams, as needed.

The application surface area should be about 5 by 7 inches (approximately the size of two palm prints). The entire contents of a unit dose packet should be applied each day. To avoid potential skin irritation, apply Divigel to the right or left upper thigh on alternating days. Do not apply Divigel on the face, breasts, or irritated skin or in or around the vagina. Allow gel to dry after application before dressing. Do not wash the application site within 1 hour after applying Divigel. Avoid contact of the gel with eyes. Wash hands after application.

3 DOSAGE FORMS AND STRENGTHS

Divigel is available in five doses of 0.25, 0.5, 0.75, 1.0, and 1.25 grams for transdermal application (corresponding to 0.25, 0.5, 0.75, 1.0, and 1.25 mg estradiol, respectively). Divigel is a clear, colorless gel, which is odorless when dry.

4 CONTRAINDICATIONS

Divigel is contraindicated in women with any of the following conditions:

- Undiagnosed abnormal genital bleeding [see Warning and Precautions (5.2)]
- Breast cancer or history of breast cancer [see Warning and Precautions (5.2)]
- Estrogen-dependent neoplasia [see Warning and Precautions (5.2)]
- Active DVT, PE, or history of these conditions [see Warning and Precautions (5.1)]
- Active arterial thromboembolic disease (e.g., stroke and MI), or a history of these conditions [see Warning and Precautions (5.1)]
- Known anaphylactic reaction, angioedema, or hypersensitivity to Divigel
- Hepatic impairment or disease
- Protein C, protein S, or antithrombin deficiency, or other known thrombophilic disorders

5 WARNINGS AND PRECAUTIONS

5.1 Cardiovascular Disorders

Increased risks of stroke and DVT are reported with estrogen-alone therapy. Increased risk of PE, DVT, stroke and MI are reported with estrogen plus progestin therapy.

Immediately discontinue estrogen with or without progestogen therapy if any of these occur or are suspected.

Manage appropriately any risk factors for arterial vascular disease (e.g., hypertension, diabetes mellitus, tobacco use, hypercholesterolemia, and obesity) and/or venous thromboembolism (VTE) (e.g., personal history or family history of VTE, obesity, and systemic lupus erythematosus).

Stroke

The WHI estrogen-alone substudy reported a statistically significant increased risk of stroke in women 50 to 79 years of age receiving daily CE (0.625 mg)-alone compared to women in the same age group receiving placebo (45 versus 33 strokes per 10,000 women-years, respectively). The increase in risk was demonstrated in year 1 and persisted [see Clinical Studies (14.2)]. Immediately discontinue estrogen-alone therapy if a stroke occurs or is suspected.

Subgroup analyses of women 50 to 59 years of age suggest no increased risk of stroke for those women receiving CE (0.625 mg)-alone versus those receiving placebo (18 versus 21 per 10,000 women-years).^1

The WHI estrogen plus progestin substudy reported a statistically significant increased risk of stroke in women 50 to 79 years of age receiving daily CE (0.625 mg) plus MPA (2.5 mg) compared to women in the same age group receiving placebo (33 versus 25 per 10,000 women-years, respectively) [see Clinical Studies (14.2)]. The increase in risk was demonstrated after the first year and persisted.^1 Immediately discontinue estrogen plus progestogen therapy if a stroke occurs or is suspected.

Coronary Heart Disease

The WHI estrogen-alone substudy reported no overall effect on coronary heart disease (CHD) events (defined as nonfatal MI, silent MI, or CHD death) in women receiving estrogen-alone compared to placebo^2 [see Clinical Studies (14.2)].

Subgroup analyses of women 50 to 59 years of age, who were less than 10 years since menopause, suggest a reduction (not statistically significant) of CHD events in those women receiving daily CE (0.625 mg)-alone compared to placebo (8 versus 16 per 10,000 women-years).^1

The WHI estrogen plus progestin substudy reported an increased risk (not statistically significant) of CHD events in those women receiving daily CE (0.625 mg) plus MPA (2.5 mg) compared to women receiving placebo (41 versus 34 per 10,000 women-years).^1 An increase in relative risk was demonstrated in year 1, and a trend toward decreasing relative risk was reported in years 2 through 5 [see Clinical Studies (14.2)].

In postmenopausal women with documented heart disease (n=2,763), average 66.7 years of age, in a controlled clinical trial of secondary prevention of cardiovascular disease [Heart and Estrogen/Progestin Replacement Study (HERS)], treatment with daily CE (0.625 mg) plus MPA (2.5 mg) demonstrated no cardiovascular benefit. During an average follow-up of 4.1 years, treatment with CE plus MPA did not reduce the overall rate of CHD events in postmenopausal women with established coronary heart disease. There were more CHD events in the CE plus MPA-treated group than in the placebo group in year 1, but not during the subsequent years. Two thousand, three hundred and twenty-one (2,321) women from the original HERS trial agreed to participate in an open label extension of HERS, HERS II. Average follow-up in HERS II was an additional 2.7 years, for a total of 6.8 years overall. Rates of CHD events were comparable among women in the CE (0.625 mg) plus MPA (2.5 mg) group and the placebo group in HERS, HERS II, and overall.

Venous Thromboembolism

In the WHI estrogen-alone substudy, the risk of VTE (DVT and PE) was increased for women receiving daily CE (0.625 mg)-alone compared to placebo (30 versus 22 per 10,000 women-years), although only the increased risk of DVT reached statistical significance (23 versus 15 per 10,000 women-years). The increase in VTE risk was demonstrated during the first 2 years^3 [see Clinical Studies (14.2)]. Immediately discontinue estrogen-alone therapy if a VTE occurs or is suspected.

The WHI estrogen plus progestin substudy reported a statistically significant 2-fold greater rate of VTE in women receiving daily CE (0.625 mg) plus MPA (2.5 mg) compared to women receiving placebo (35 versus 17 per 10,000 women-years). Statistically significant increases in risk for both DVT (26 versus 13 per 10,000 women-years) and PE (18 versus 8 per 10,000 women-years) were also demonstrated. The increase in VTE risk was demonstrated during the first year and persisted^4 [see Clinical Studies (14.2)]. Immediately discontinue estrogen plus progestogen therapy if a VTE occurs or is suspected.

If feasible, discontinue estrogens at least 4 to 6 weeks before surgery of the type associated with an increased risk of thromboembolism, or during periods of prolonged immobilization.

5.2 Malignant Neoplasms

Endometrial Cancer

An increased risk of endometrial cancer has been reported with the use of unopposed estrogen therapy in a woman with a uterus. The reported endometrial cancer risk among unopposed estrogen users is about 2- to 12-fold greater than in non-users, and appears dependent on duration of treatment and on estrogen dose. Most studies show no significant increased risk associated with use of estrogens for less than 1 year. The greatest risk appears associated with prolonged use, with increased risk of 15- to 24-fold for 5 to 10 years or more and this risk has been shown to persist for at least 8 to 15 years after estrogen therapy is discontinued.

Clinical surveillance of all women using estrogen-alone or estrogen plus progestogen therapy is important. Perform adequate diagnostic measures, including directed or random endometrial sampling when indicated, to rule out malignancy in postmenopausal women with undiagnosed persistent or recurring abnormal genital bleeding with unknown etiology. There is no evidence that the use of natural estrogens results in a different endometrial risk profile than synthetic estrogens of equivalent estrogen dose. Adding a progestogen to postmenopausal estrogen therapy in postmenopausal women has been shown to reduce the risk of endometrial hyperplasia, which may be a precursor to endometrial cancer.

Breast Cancer

The WHI substudy of daily CE (0.625 mg)-alone provided information about breast cancer in estrogen-alone users. In the WHI estrogen-alone substudy, after an average follow-up of 7.1 years, daily CE-alone was not associated with an increased risk of invasive breast cancer [relative risk (RR) 0.80] compared to placebo^5 [see Clinical Studies (14.2)].

After a mean follow-up of 5.6 years, the WHI substudy of daily CE (0.625 mg) plus MPA (2.5 mg) reported an increased risk of invasive breast cancer in women who took daily CE plus MPA compared to placebo. In this substudy, prior use of estrogen-alone or estrogen plus progestin therapy was reported by 26 percent of the women. The relative risk of invasive breast cancer was 1.24, and the absolute risk was 41 versus 33 cases per 10,000 women-years, for CE plus MPA compared with placebo. Among women who reported prior use of hormone therapy, the relative risk of invasive breast cancer was 1.86, and the absolute risk was 46 versus 25 cases per 10,000 women-years, for CE plus MPA compared with placebo. Among women who reported no prior use of hormone therapy, the relative risk of invasive breast cancer was 1.09, and the absolute risk was 40 versus 36 cases per 10,000 women-years for CE plus MPA compared with placebo. In the same substudy, invasive breast cancers were larger, were more likely to be node positive, and were diagnosed at a more advanced stage in the CE (0.625 mg) plus MPA (2.5 mg) group compared with the placebo group. Metastatic disease was rare, with no apparent difference between the two groups. Other prognostic factors such as histologic subtype, grade and hormone receptor status did not differ between the groups^6 [see Clinical Studies (14.2)].

Consistent with the WHI clinical trial, observational studies have also reported an increased risk of breast cancer with estrogen plus progestin therapy, and a smaller increase in the risk for breast cancer with estrogen-alone therapy, after several years of use. One large meta-analysis of prospective cohort studies reported increased risks that were dependent upon duration of use and could last up to >10 years after discontinuation of estrogen plus progestin therapy and estrogen-alone therapy. Extension of the WHI trials also demonstrated increased breast cancer risk associated with estrogen plus progestin therapy. Observational studies also suggest that the risk of breast cancer was greater, and became apparent earlier, with estrogen plus progestin therapy as compared to estrogen-alone therapy.

These studies have not generally found significant variation in the risk of breast cancer among different estrogen plus progestin combinations, doses, or routes of administration.

The use of estrogen-alone and estrogen plus progestin has been reported to result in an increase in abnormal mammograms requiring further evaluation.

Have all women receive yearly breast examinations by a healthcare provider and perform monthly breast self-examinations. In addition, base the scheduling of mammography examinations on patient age, risk factors, and prior mammogram results.

Ovarian Cancer

The CE plus MPA substudy of WHI reported that estrogen plus progestin increased the risk of ovarian cancer. After an average follow-up of 5.6 years, the relative risk for CE plus MPA versus placebo was 1.58 (95 percent CI, 0.77–3.24), but was not statistically significant. The absolute risk for CE plus MPA versus placebo was 4 versus 3 cases per 10,000 women-years.^7

A meta-analysis of 17 prospective and 35 retrospective epidemiology studies found that women who used hormonal therapy for menopausal symptoms had an increased risk for ovarian cancer. The primary analysis, using case-control comparisons, included 12,110 cancer cases from the 17 prospective studies. The relative risks associated with current use of hormonal therapy was 1.41 (95% confidence interval [CI] 1.32 to 1.50); there was no difference in the risk estimates by duration of the exposure (less than 5 years [median of 3 years] vs. greater than 5 years [median of 10 years] of use before the cancer diagnosis). The relative risk associated with combined current and recent use (discontinued use within 5 years before cancer diagnosis) was 1.37 (95% CI 1.27-1.48), and the elevated risk was significant for both estrogen-alone and estrogen plus progestin products. The exact duration of hormone therapy use associated with an increased risk of ovarian cancer, however, is unknown.

5.3 Probable Dementia

In the WHI Memory Study (WHIMS) estrogen-alone ancillary study, a population of 2,947 hysterectomized women 65 to 79 years of age was randomized to daily CE (0.625 mg)-alone or placebo.

After an average follow-up of 5.2 years, 28 women in the estrogen-alone group and 19 women in the placebo group were diagnosed with probable dementia. The relative risk of probable dementia for CE- alone versus placebo was 1.49 (95 percent CI, 0.83–2.66). The absolute risk of probable dementia for CE-alone versus placebo was 37 versus 25 cases per 10,000 women-years^8 [see Use in Specific Populations (8.5), and Clinical Studies (14.3)].

In the WHIMS estrogen plus progestin ancillary study, a population of 4,532 postmenopausal women 65 to 79 years of age was randomized to daily CE (0.625 mg) plus MPA (2.5 mg) or placebo.

After an average follow-up of 4 years, 40 women in the CE plus MPA group and 21 women in the placebo group were diagnosed with probable dementia. The relative risk of probable dementia for CE plus MPA versus placebo was 2.05 (95 percent CI, 1.21–3.48). The absolute risk of probable dementia for CE plus MPA versus placebo was 45 versus 22 cases per 10,000 women-years^8 [see Use in Specific Populations (8.5), and Clinical Studies (14.3)].

When data from the two populations in the WHIMS estrogen-alone and estrogen plus progestin ancillary studies were pooled as planned in the WHIMS protocol, the reported overall relative risk for probable dementia was 1.76 (95 percent CI, 1.19–2.60). Since both ancillary studies were conducted in women 65 to 79 years of age, it is unknown whether these findings apply to younger postmenopausal women^8 [see Use in Specific Populations (8.5), and Clinical Studies (14.3)].

5.4 Gallbladder Disease

A 2- to 4-fold increase in the risk of gallbladder disease requiring surgery in postmenopausal women receiving estrogens has been reported.

5.5 Hypercalcemia

Estrogen administration may lead to severe hypercalcemia in women with breast cancer and bone metastases. Discontinue estrogens, including Divigel, if hypercalcemia occurs, and take appropriate measures to reduce the serum calcium level.

5.6 Visual Abnormalities

Retinal vascular thrombosis has been reported in patients receiving estrogens. Discontinue Divigel pending examination if there is sudden partial or complete loss of vision, or a sudden onset of proptosis, diplopia, or migraine. Permanently discontinue estrogens, including Divigel, if examination reveals papilledema or retinal vascular lesions.

5.7 Addition of a Progestogen When a Woman Has Not Had a Hysterectomy

Studies of the addition of a progestogen for 10 or more days of a cycle of estrogen administration, or daily with estrogen in a continuous regimen, have reported a lowered incidence of endometrial hyperplasia than would be induced by estrogen treatment alone. Endometrial hyperplasia may be a precursor to endometrial cancer.

There are, however, possible risks that may be associated with the use of progestogens with estrogens compared to estrogen-alone regimens. These include an increased risk of breast cancer.

5.8 Elevated Blood Pressure

In a small number of case reports, substantial increases in blood pressure have been attributed to idiosyncratic reactions to estrogens. In a large, randomized, placebo-controlled clinical trial, a generalized effect of estrogens on blood pressure was not seen.

5.9 Exacerbation of Hypertriglyceridemia

In women with pre-existing hypertriglyceridemia, estrogen therapy may be associated with elevations of plasma triglycerides leading to pancreatitis. Discontinue Divigel if pancreatitis occurs.

5.10 Hepatic Impairment and/or Past History of Cholestatic Jaundice

Estrogens may be poorly metabolized in women with hepatic impairment. Exercise caution in any woman with a history of cholestatic jaundice associated with past estrogen use or with pregnancy. In the case of recurrence of cholestatic jaundice, discontinue Divigel.

5.11 Exacerbation of Hypothyroidism

Estrogen administration leads to increased thyroid-binding globulin (TBG) levels. Women with normal thyroid function can compensate for the increased TBG by making more thyroid hormone, thus maintaining free T4 and T3 serum concentrations in the normal range. Women dependent on thyroid hormone replacement therapy who are also receiving estrogens may require increased doses of their thyroid replacement therapy. Monitor thyroid function in these women during treatment with Divigel to maintain their free thyroid hormone levels in an acceptable range.

5.12 Fluid Retention

Estrogens may cause some degree of fluid retention. Monitor any woman with a condition(s) that might predispose her to fluid retention, such as a cardiac or renal impairment. Discontinue estrogen-alone therapy, including Divigel, with evidence of medically concerning fluid retention.

5.13 Hypocalcemia

Estrogen-induced hypocalcemia may occur in women with hypoparathyroidism. Consider whether the benefits of estrogen therapy outweigh the risks in such women.

5.14 Exacerbation of Endometriosis

A few cases of malignant transformation of residual endometrial implants have been reported in women treated post-hysterectomy with estrogen-alone therapy. Consider the addition of a progestogen therapy for a woman known to have residual endometriosis post-hysterectomy.

5.15 Hereditary Angioedema

Exogenous estrogens may exacerbate symptoms of angioedema in women with hereditary angioedema. Consider whether the benefits of estrogen therapy, including Divigel, outweigh the risks in such women.

5.16 Exacerbation of Other Conditions

Estrogen therapy, including Divigel, may cause an exacerbation of asthma, diabetes mellitus, epilepsy, migraine, porphyria, systemic lupus erythematosus, and hepatic hemangiomas. Consider whether the benefits of estrogen therapy outweigh the risks in women with such conditions.

5.17 Photosensitivity

The effects of direct sun exposure to Divigel application sites have not been evaluated in clinical trials.

5.18 Application of Sunscreen and Topical Solutions

Studies conducted using other approved topical estrogen gel products have shown that sunscreens have the potential for changing the systemic exposure of topically applied estrogen gels.

The effect of sunscreens and other topical lotions on the systemic exposure of Divigel has not been evaluated in clinical trials.

5.19 Flammability of Alcohol-Based Gels

Alcohol based gels are flammable. Avoid fire, flame, or smoking until Divigel has dried.

Occlusion of the area where the topical drug product is applied with clothing or other barriers is not recommended until Divigel has completely dried.

5.20 Potential for Estradiol Transfer and Effects of Washing

There is a potential for drug transfer from one individual to the other following physical contact of Divigel application sites. In a study to evaluate transferability to males from their female contacts, there was some elevation of estradiol levels over baseline in the male subjects; however, the degree of transferability in this study was inconclusive. Women are advised to avoid skin contact with other persons until the gel is completely dried. The site of application should be covered (clothed) after drying.

Washing the application site with soap and water 1 hour after application resulted in a 30 to 38 percent decrease in the mean total 24-hour exposure to estradiol. Therefore, women should refrain from washing the application site for at least one hour after application.

5.21 Laboratory Tests

Serum follicle stimulating hormone (FSH) and estradiol levels are not useful in the management of moderate to severe vasomotor symptoms.

5.22 Drug-Laboratory Test Interactions

- Accelerated prothrombin time, partial thromboplastin time, and platelet aggregation time; increased platelet count; increased factors II, VII antigen, VIII antigen, VIII coagulant activity, IX, X, XII, VII-X complex, II-VII-X complex, and beta-thromboglobulin; decreased levels of anti-factor Xa and antithrombin III, decreased antithrombin III activity; increased levels of fibrinogen and fibrinogen activity; increased plasminogen antigen and activity.
- Increased thyroid binding globulin (TBG) levels leading to increased circulating total thyroid hormone levels, as measured by protein-bound iodine (PBI), T4 levels (by column or by radioimmunoassay) or T3 levels by radioimmunoassay. T3 resin uptake is decreased, reflecting the elevated TBG. Free T4 and free T3 concentrations are unaltered. Women on thyroid replacement therapy may require higher doses of thyroid hormone.
- Other binding proteins may be elevated in serum, for example, corticosteroid binding globulin (CBG), sex hormone-binding globulin (SHBG), leading to increased total circulating corticosteroids and sex steroids, respectively. Free hormone concentrations, such as testosterone and estradiol, may be decreased. Other plasma proteins may be increased (angiotensinogen/renin substrate, alpha-l-antitrypsin, ceruloplasmin).
- Increased plasma high-density lipoprotein (HDL) and HDL2 cholesterol subfraction concentrations, reduced low-density lipoprotein (LDL) cholesterol concentration, increased triglyceride levels.
- Impaired glucose tolerance.

6 ADVERSE REACTIONS

The following serious adverse reactions are discussed elsewhere in the labeling:

- Cardiovascular Disorders [see Boxed Warning, Warnings and Precautions (5.1)].
- Malignant Neoplasms [see Boxed Warning, Warnings and Precautions (5.2)].

6.1 Clinical Trials Experience

Because clinical trials are conducted under widely varying conditions, adverse reaction rates observed in the clinical trials of a drug cannot be directly compared to rates in the clinical trials of another drug and may not reflect the rates observed in practice.

Divigel was studied at doses of 0.25, 0.5 and 1.0 gram per day in a 12-week, double-blind, placebo-controlled study that included a total of 495 postmenopausal women (86.5 percent Caucasian). The adverse reactions that occurred at a rate greater than 5 percent and greater than placebo in any of the treatment groups are summarized in Table 1.

In a 12-week placebo-controlled study of Divigel, application site reactions were seen in <1 percent of participating women.

6.2 Postmarketing Experience

The following adverse reactions have been identified during post-approval use of Divigel. Because these reactions are reported voluntarily from a population of uncertain size, it is not always possible to reliably estimate their frequency or establish a causal relationship to drug exposure.

Genitourinary System

Amenorrhea, dysmenorrhea, ovarian cyst, vaginal discharge

Breasts

Gynecomastia

Cardiovascular

Palpitations, ventricular extrasystoles

Gastrointestinal

Flatulence

Skin

Rash pruritic, urticaria

Eyes

Retinal vein occlusion

Central Nervous System

Tremor

Miscellaneous

Arthralgia, application site rash, asthenia, chest discomfort, fatigue, feeling abnormal, heart rate increased, insomnia, malaise, muscle spasms, pain in extremity, weight increased

7 DRUG INTERACTIONS

In vitro and in vivo studies have shown that estrogens are metabolized partially by cytochrome P450 3A4 (CYP3A4). Therefore, inducers or inhibitors of CYP3A4 may affect estrogen drug metabolism. Inducers of CYP3A4, such as St. John's wort (Hypericum perforatum) preparations, phenobarbital, carbamazepine, and rifampin, may reduce plasma concentrations of estrogens, possibly resulting in a decrease in therapeutic effects and/or changes in the uterine bleeding profile. Inhibitors of CYP3A4, such as erythromycin, clarithromycin, ketoconazole, itraconazole, ritonavir, and grapefruit juice, may increase plasma concentrations of estrogens and result in adverse reactions.

8 USE IN SPECIFIC POPULATIONS

8.1 Pregnancy

Risk Summary

Divigel is not indicated for use in pregnant women. There are no data with the use of Divigel in pregnant women; however, epidemiologic studies and meta-analyses have not found an increased risk of genital or nongenital birth defects (including cardiac anomalies and limb-reduction defects) following exposure to combined hormonal contraceptives (estrogen and progestins) before conception or during early pregnancy.

In the U.S. general population, the estimated background risk of major birth defects and miscarriage in clinically recognized pregnancies is 2% to 4% and 15% to 20%, respectively.

8.2 Lactation

Risk Summary

Estrogens are present in human milk and can reduce milk production in breast-feeding women. This reduction can occur at any time but is less likely to occur once breast-feeding is well established.

The developmental and health benefits of breastfeeding should be considered along with the mother's clinical need for Divigel and any potential adverse effects on the breastfed child from Divigel or from the underlying maternal condition.

8.4 Pediatric Use

Divigel is not indicated for use in pediatric patients. Clinical studies have not been conducted in the pediatric population.

8.5 Geriatric Use

There have not been sufficient numbers of geriatric women involved in studies utilizing Divigel to determine whether those over 65 years of age differ from younger subjects in their response to Divigel.

The Women's Health Initiative Studies

In the WHI estrogen-alone substudy (daily CE [0.625 mg]-alone versus placebo), there was a higher relative risk of stroke in women greater than 65 years of age [see Warnings and Precautions (5.1), and Clinical Studies (14.2)].

In the WHI estrogen plus progestin substudy (daily CE [0.625 mg] plus MPA [2.5 mg] versus placebo), there was a higher relative risk of nonfatal stroke and invasive breast cancer in women greater than 65 years of age [see Warnings and Precautions (5.1, 5.2), and Clinical Studies (14.2)].

The Women's Health Initiative Memory Study

In the WHIMS ancillary studies of postmenopausal women 65 to 79 years of age, there was an increased risk of developing probable dementia in women receiving estrogen-alone or estrogen plus progestin when compared to placebo [see Warnings and Precautions (5.3), and Clinical Studies (14.3)].

Since both ancillary studies were conducted in women 65 to 79 years of age, it is unknown whether these findings apply to younger postmenopausal women^8 [see Warnings and Precautions (5.3), and Clinical Studies (14.3)].

10 OVERDOSAGE

Overdosage of estrogen may cause nausea and vomiting, breast tenderness, abdominal pain, drowsiness and fatigue, and withdrawal bleeding in women. Treatment of overdose consists of discontinuation of Divigel therapy with institution of appropriate symptomatic care.

11 DESCRIPTION

Divigel (estradiol gel) 0.1 percent, is a clear, colorless gel, which is odorless when dry. It is designed to deliver sustained circulating concentrations of estradiol when applied once daily to the skin. The gel is applied to a small area (200 cm^2) of the thigh in a thin layer. Divigel is available in five doses of 0.25, 0.5, 0.75, 1.0, and 1.25 grams for topical application (corresponding to 0.25, 0.5, 0.75, 1.0, and 1.25 mg estradiol, respectively).

The active component of the topical gel is estradiol.

Estradiol is a white crystalline powder, chemically described as estra-1,3,5(10)-triene-3,17ß-diol. It has an empirical formula of C18H24O2 and molecular weight of 272.39. The structural formula is:

Divigel Chemical Structure

The remaining components of the gel (carbomer, ethanol, propylene glycol, purified water, and triethanolamine) are pharmacologically inactive.

12 CLINICAL PHARMACOLOGY

12.1 Mechanism of Action

Endogenous estrogens are largely responsible for the development and maintenance of the female reproductive system and secondary sexual characteristics. Although circulating estrogens exist in a dynamic equilibrium of metabolic interconversions, estradiol is the principal intracellular human estrogen and is substantially more potent than its metabolites, estrone and estriol, at the receptor level.

The primary source of estrogen in normally cycling adult women is the ovarian follicle, which secretes 70 to 500 mcg of estradiol daily, depending on the phase of the menstrual cycle. After menopause, most endogenous estrogen is produced by conversion of androstenedione, which is secreted by the adrenal cortex, to estrone in the peripheral tissues. Thus, estrone and the sulfate conjugated form, estrone sulfate, are the most abundant circulating estrogens in postmenopausal women.

Estrogens act through binding to nuclear receptors in estrogen-responsive tissues. To date, two estrogen receptors have been identified. These vary in proportion from tissue to tissue.

Circulating estrogens modulate the pituitary secretion of the gonadotropins, luteinizing hormone (LH) and FSH, through a negative feedback mechanism. Estrogens act to reduce the elevated levels of these hormones seen in postmenopausal women.

12.2 Pharmacodynamics

Generally, a serum estrogen concentration does not predict an individual woman’s therapeutic response to Divigel nor her risk for adverse outcomes. Likewise, exposure comparisons across different estrogen products to infer efficacy or safety for the individual woman may not be valid.

12.3 Pharmacokinetics

Absorption

Estradiol diffuses across intact skin and into the systemic circulation by a passive absorption process, with diffusion across the stratum corneum being the rate-limiting factor.

In a 14-day, Phase 1, multiple-dose study, Divigel demonstrated linear and approximately dose- proportional estradiol pharmacokinetics at steady state for both AUC0-24 and Cmax following once daily dosing to the skin of either the right or left upper thigh (Table 2).

Steady-state serum concentration of estradiol are achieved by day 12 following daily application of Divigel to the skin of the upper thigh. The mean (SD) serum estradiol levels following once daily dosing at day 14 are shown in Figure 1.

Figure 1: Mean (SD) Serum Estradiol Concentrations (Values Uncorrected for Baseline) on Day 14 Following Multiple Daily Doses of Divigel 0.1%

Figure 1

The effect of sunscreens and other topical lotions on the systemic exposure of Divigel has not been evaluated. Studies conducted using topical estrogen gel approved products have shown that sunscreens have the potential for changing the systemic exposure of topically applied estrogen gels.

Distribution

The distribution of exogenous estrogens is similar to that of endogenous estrogens. Estrogens are widely distributed in the body and are generally found in higher concentrations in the sex hormone target organs. Estrogens circulate in the blood largely bound to SHBG and albumin.

Metabolism

Exogenous estrogens are metabolized in the same manner as endogenous estrogens. Circulating estrogens exist in a dynamic equilibrium of metabolic interconversions. These transformations take place mainly in the liver. Estradiol is converted reversibly to estrone, and both can be converted to estriol, which is a major urinary metabolite. Estrogens also undergo enterohepatic recirculation via sulfate and glucuronide conjugation in the liver, biliary secretion of conjugates into the intestine, and hydrolysis in the intestine followed by reabsorption. In postmenopausal women, a significant proportion of the circulating estrogens exist as sulfate conjugates, especially estrone sulfate, which serves as a circulating reservoir for the formation of more active estrogens.

Although the clinical significance has not been determined, estradiol from Divigel does not undergo first pass metabolism and provides estradiol to estrone ratios at steady state in the range of 0.42 to 0.65.

Excretion

Estradiol, estrone, and estriol are excreted in the urine along with glucuronide and sulfate conjugates. The apparent terminal half-life for estradiol was about 10 hours following administration of Divigel.

Potential for Estradiol Transfer

The effect of estradiol transfer was evaluated in healthy postmenopausal women who topically applied 1.0 gram of Divigel (single dose) on one thigh. One and 8 hours after gel application, they engaged in direct thigh-to-arm contact with a partner for 15 minutes. While some elevation of estradiol levels over baseline was seen in the male subjects, the degree of transferability in this study was inconclusive.

Effects of Washing

The effect of application site washing on skin surface levels and serum concentrations of estradiol was determined in 16 healthy postmenopausal women after application of 1.0 gram of Divigel to a 200 cm^2 area on the thigh. Washing the application site with soap and water 1 hour after application removed all detectable amounts of estradiol from the surface of the skin and resulted in a 30 to 38 percent decrease in the mean total 24-hour exposure to estradiol.

13 NONCLINICAL TOXICOLOGY

13.1 Carcinogenesis, Mutagenesis, and Impairment of Fertility

Long-term continuous administration of natural and synthetic estrogens in certain animal species increases the frequency of carcinomas of the breast, uterus, cervix, vagina, testis and liver.

14 CLINICAL STUDIES

14.1 Effects on Vasomotor Symptoms in Postmenopausal Women

A randomized, double-blind, placebo-controlled trial evaluated the efficacy of 12-week treatment with three different daily doses of Divigel for vasomotor symptoms in 495 postmenopausal women (86.5 percent White; 10.1 percent Black) between 34 and 89 years of age (mean age 54.6) who had at least 50 moderate to severe hot flushes per week at baseline (2-week period prior to treatment). Women applied placebo, Divigel 0.25 grams (0.25 mg estradiol), Divigel 0.5 grams (0.5 mg estradiol) or Divigel 1.0 gram (1.0 mg estradiol) once daily to the thigh. Reductions in both the median daily frequency and the median daily severity of moderate to severe hot flushes were statistically significant for the 0.5 grams per day and the 1.0 gram per day Divigel doses when compared to placebo at week 4. Statistically significant reductions in both the median daily frequency and the median daily severity of moderate to severe hot flushes for the Divigel 0.25 grams per day dose when compared to placebo were delayed to week 7. There were statistically significant reductions in median daily frequency and severity of hot flushes for all three Divigel doses (0.25 grams per day, 0.5 grams per day and 1.0 gram per day) compared to placebo at week 12. See Table 3 for results.

14.2 Women's Health Initiative Studies

The WHI enrolled approximately 27,000 predominantly healthy postmenopausal women in two substudies to assess the risks and benefits of daily oral CE (0.625 mg)-alone or in combination with MPA (2.5 mg) compared to placebo in the prevention of certain chronic diseases. The primary endpoint was the incidence of CHD (defined as nonfatal MI, silent MI and CHD death), with invasive breast cancer as the primary adverse outcome. A "global index" included the earliest occurrence of CHD, invasive breast cancer, stroke, PE, endometrial cancer (only in the CE plus MPA substudy), colorectal cancer, hip fracture, or death due to other cause. These substudies did not evaluate the effects of CE- alone or CE plus MPA on menopausal symptoms.

WHI Estrogen-Alone Substudy

The WHI estrogen-alone substudy was stopped early because an increased risk of stroke was observed, and it was deemed that no further information would be obtained regarding the risks and benefits of estrogen-alone in predetermined primary endpoints. Results of the estrogen-alone substudy, which included 10,739 women (average 63 years of age, range 50 to 79; 75.3 percent White, 15.1 percent Black, 6.1 percent Hispanic, 3.6 percent Other), after an average follow-up of 7.1 years are presented in Table 4.

For those outcomes included in the WHI "global index" that reached statistical significance, the absolute excess risk per 10,000 women-years in the group treated with CE-alone was 12 more strokes, while the absolute risk reduction per 10,000 women-years was 7 fewer hip fractures.^9 The absolute excess risk of events included in the "global index" was a nonsignificant 5 events per 10,000 women- years. There was no difference between the groups in terms of all-cause mortality.

No overall difference for primary CHD events (nonfatal MI, silent MI and CHD death) and invasive breast cancer incidence in women receiving CE-alone compared with placebo was reported in final centrally adjudicated results from the estrogen-alone substudy, after an average follow-up of 7.1 years. See Table 4.

Centrally adjudicated results for stroke events from the estrogen-alone substudy, after an average follow-up of 7.1 years, reported no significant difference in distribution of stroke subtype or severity, including fatal strokes, in women receiving CE-alone compared to placebo. Estrogen-alone increased the risk for ischemic stroke, and this excess risk was present in all subgroups of women examined.^10

Timing of the initiation of estrogen-alone therapy relative to the start of menopause may affect the overall risk benefit profile. The WHI estrogen-alone substudy stratified by age showed in women 50 to 59 years of age a non-significant trend toward reduced risk for CHD [hazard ratio (HR) 0.63 (95 percent CI, 0.36–1.09)] and overall mortality [HR 0.71 (95 percent CI, 0.46–1.11)].

WHI Estrogen Plus Progestin Substudy

The WHI estrogen plus progestin substudy was stopped early. According to the predefined stopping rule, after an average follow-up of 5.6 years of treatment, the increased risk of breast cancer and cardiovascular events exceeded the specified benefits included in the "global index." The absolute excess risk of events included in the "global index" was 19 per 10,000 women-years.

For those outcomes included in the WHI "global index" that reached statistical significance after 5.6 years of follow-up, the absolute excess risks per 10,000 women-years in the group treated with CE plus MPA were 7 more CHD events, 8 more strokes, 10 more PEs, and 8 more invasive breast cancers, while the absolute risk reductions per 10,000 women-years were 6 fewer colorectal cancers and 5 fewer hip fractures.

Results of the CE plus MPA substudy, which included 16,608 women (average 63 years of age, range 50 to 79; 83.9 percent White, 6.8 percent Black, 5.4 percent Hispanic, 3.9 percent Other), are presented in Table 5. These results reflect centrally adjudicated data after an average follow-up of 5.6 years.

Timing of the initiation of estrogen plus progestin therapy relative to the start of menopause may affect the overall risk benefit profile. The WHI estrogen plus progestin substudy stratified for age showed in women 50 to 59 years of age a non-significant trend toward reduced risk for overall mortality [HR 0.69 (95 percent CI, 0.44–1.07)].

14.3 Women's Health Initiative Memory Study

The WHIMS estrogen-alone ancillary study of WHI enrolled 2,947 predominantly healthy hysterectomized postmenopausal women 65 to 79 years of age (45 percent were 65 to 69 year of age, 36 percent were 70 to 74 years of age, and 19 percent were 75 years of age and older) to evaluate the effects of daily CE (0.625 mg)-alone on the incidence of probable dementia (primary outcome) compared to placebo.

After an average follow-up of 5.2 years, the relative risk of probable dementia for CE-alone versus placebo was 1.49 (95 percent CI, 0.83–2.66). The absolute risk of probable dementia for CE-alone versus placebo was 37 versus 25 cases per 10,000 women-years. Probable dementia as defined in this study included Alzheimer disease (AD), vascular dementia (VaD) and mixed type (having features of both AD and VaD). The most common classification of probable dementia in the treatment group and the placebo group was AD. Since the ancillary study was conducted in women 65 to 79 years of age, it is unknown whether these findings apply to younger postmenopausal women [see Warnings and Precautions (5.3), and Use in Specific Populations (8.5)].

The WHIMS estrogen plus progestin ancillary study enrolled 4,532 predominantly healthy postmenopausal women 65 years of age and older (47 percent were 65 to 69 years of age, 35 percent were 70 to 74 years of age, and 18 percent were 75 years of age and older) to evaluate the effects of daily CE (0.625 mg) plus MPA (2.5 mg) on the incidence of probable dementia (primary outcome) compared to placebo.

After an average follow-up of 4 years, the relative risk of probable dementia for CE plus MPA versus placebo was 2.05 (95 percent CI, 1.21–3.48). The absolute risk of probable dementia for CE plus MPA versus placebo was 45 versus 22 per 10,000 women-years. Probable dementia as defined in this study included AD, VaD and mixed type (having features of both AD and VaD). The most common classification of probable dementia in the treatment group and the placebo group was AD. Since the ancillary study was conducted in women 65 to 79 years of age, it is unknown whether these findings apply to younger postmenopausal women [see Warnings and Precautions (5.3), and Use in Specific Populations (8.5)].

When data from the two populations were pooled as planned in the WHIMS protocol, the reported overall relative risk for probable dementia was 1.76 (95 percent CI, 1.19–2.60). Differences between groups became apparent in the first year of treatment. It is unknown whether these findings apply to younger postmenopausal women [see Warnings and Precautions (5.3), and Use in Specific Populations (8.5)].

15 REFERENCES

1. Rossouw JE, et al. Postmenopausal Hormone Therapy and Risk of Cardiovascular Disease by Age and Years Since Menopause. JAMA. 2007;297:1465–1477.
2. Hsia J, et al. Conjugated Equine Estrogens and Coronary Heart Disease. Arch Int Med. 2006;166:357–365.
3. Curb JD, et al. Venous Thrombosis and Conjugated Equine Estrogen in Women Without a Uterus. Arch Int Med. 2006;166:772–780.
4. Cushman M, et al. Estrogen Plus Progestin and Risk of Venous Thrombosis. JAMA. 2004;292:1573–1580.
5. Stefanick ML, et al. Effects of Conjugated Equine Estrogens on Breast Cancer and Mammography Screening in Postmenopausal Women With Hysterectomy. JAMA. 2006;295:1647–1657.
6. Chlebowski RT, et al. Influence of Estrogen Plus Progestin on Breast Cancer and Mammography in Healthy Postmenopausal Women. JAMA. 2003;289:3234–3253.
7. Anderson GL, et al. Effects of Estrogen Plus Progestin on Gynecologic Cancers and Associated Diagnostic Procedures. JAMA. 2003;290:1739–1748.
8. Shumaker SA, et al. Conjugated Equine Estrogens and Incidence of Probable Dementia and Mild Cognitive Impairment in Postmenopausal Women. JAMA. 2004;291:2947–2958.
9. Jackson RD, et al. Effects of Conjugated Equine Estrogen on Risk of Fractures and BMD in Postmenopausal Women With Hysterectomy: Results From the Women's Health Initiative Randomized Trial. J Bone Miner Res. 2006;21:817–828.
10. Hendrix SL, et al. Effects of Conjugated Equine Estrogen on Stroke in the Women's Health Initiative. Circulation. 2006;113:2425–2434.

16 HOW SUPPLIED/STORAGE AND HANDLING

16.1 How Supplied

Divigel (estradiol gel) 0.1% is a clear, colorless, smooth, opalescent gel supplied in single-dose foil packets of 0.25, 0.5, 0.75, 1.0, and 1.25 grams, corresponding to 0.25, 0.5, 0.75, 1.0, and 1.25 mg estradiol, respectively.

NDC 68025-065-30, carton of 30 packets, 0.25 mg estradiol per single-dose foil packet

NDC 68025-066-30, carton of 30 packets, 0.5 mg estradiol per single-dose foil packet

NDC 68025-083-30, carton of 30 packets, 0.75 mg estradiol per single-dose foil packet

NDC 68025-067-30, carton of 30 packets, 1.0 mg estradiol per single-dose foil packet

NDC 68025-086-30, carton of 30 packets, 1.25 mg estradiol per single-dose foil packet

Keep out of the reach of children.

16.2 Storage and Handling

Store at 20 to 25°C (68 to 77°F). Excursions permitted to 15 to 30°C (59 to 86°F). [See USP Controlled Room Temperature.]

17 PATIENT COUNSELING INFORMATION

Advise women to read the FDA-approved patient labeling (Patient Information and Instructions for Use).

Vaginal Bleeding

Inform postmenopausal women to report any vaginal bleeding to their healthcare provider as soon as possible [see Warnings and Precautions (5.2)].

Unintentional Secondary Exposure to Divigel

Inform women about the possibility of secondary exposure to Divigel:

- Apply Divigel as directed and keep children from contacting exposed application site(s). If direct contact with the application site occurs, wash the contact area thoroughly with soap and water.
- Look for signs of unexpected sexual development, such as breast mass or increased breast size in prepubertal children.
- If signs of unintentional secondary exposure are noticed:
  - Have the child(ren) evaluated by a healthcare provider.
  - Have women contact their healthcare provider to discuss the appropriate use and handling of Divigel when around children.
- Pets may also be unintentionally exposed to Divigel if above precautions are not followed.

Possible Serious Adverse Reactions with Estrogen-Alone Therapy

Inform postmenopausal women of possible serious adverse reactions of estrogen-alone therapy including Cardiovascular Disorders, Malignant Neoplasms, and Probable Dementia [see Warnings and Precautions (5.1, 5.2, 5.3)].

Possible Less Serious but Common Adverse Reactions with Estrogen-Alone Therapy

Inform postmenopausal women of possible less serious but common adverse reactions of estrogen-alone therapy such as headaches, breast pain and tenderness, nausea and vomiting.

151083-12

PATIENT INFORMATION

DIVIGEL® (dih-vih-jel)

(estradiol gel) 0.1%

Read this Patient Information leaflet before you start using Divigel and each time you get a refill. There may be new information. This information does not take the place of talking to your healthcare provider about your menopausal symptoms or your treatment.

WHAT IS THE MOST IMPORTANT INFORMATION I SHOULD KNOW ABOUT Divigel (AN ESTROGEN HORMONE)?

- Using estrogen-alone increases your chance of getting cancer of the uterus (womb).
- Report any unusual vaginal bleeding right away while you are using Divigel. Vaginal bleeding after menopause may be a warning sign of cancer of the uterus (womb). Your healthcare provider should check any unusual vaginal bleeding to find out the cause.
- Do not use estrogen-alone to prevent heart disease, heart attacks, strokes or dementia (decline of brain function)
- Using estrogen-alone may increase your chances of getting strokes or blood clots
- Using estrogen-alone may increase your chance of getting dementia, based on a study of women 65 years of age and older
- Do not use estrogens with progestogens to prevent heart disease, heart attacks, strokes or dementia
- Using estrogens with progestogens may increase your chances of getting heart attacks, strokes, breast cancer, or blood clots
- Using estrogens with progestogens may increase your chance of getting dementia, based on a study of women 65 years of age or older
- Only one estrogen-alone product and dose have been shown to increase your chances of getting strokes, blood clots, and dementia. Only one estrogen with progestogen product and dose have been shown to increase your chances of getting heart attacks, strokes, breast cancer, blood clots, and dementia.

Because other products and doses have not been studied in the same way, it is not known how the use of Divigel will affect your chances of these conditions. You and your healthcare provider should talk regularly about whether you still need treatment with Divigel.

What is Divigel?

Divigel is a prescription medicine that contains estradiol (an estrogen hormone). Divigel is a clear, colorless, smooth gel that is odorless when dry. When applied to the skin, estradiol is absorbed through the skin into the bloodstream.

What is Divigel used for?

Divigel is used after menopause to:

- Reduce moderate to severe hot flashes

Estrogens are hormones made by a woman's ovaries. The ovaries normally stop making estrogens when a woman is between 45 to 55 years old. This drop in body estrogen levels causes the "change of life" or menopause (the end of monthly menstrual periods). Sometimes, both ovaries are removed during an operation before natural menopause takes place. The sudden drop in estrogen levels causes "surgical menopause."

When the estrogen levels begin dropping, some women develop very uncomfortable symptoms, such as feelings of warmth in the face, neck, and chest, or sudden intense feelings of heat and sweating ("hot flashes" or "hot flushes"). In some women, the symptoms are mild, and they will not need estrogens. In other women, symptoms can be more severe.

Who should not use Divigel?

Do not start using Divigel if you:

- have any unusual vaginal bleeding

Vaginal bleeding after menopause may be a warning sign of cancer of the uterus (womb). Your healthcare provider should check any unusual vaginal bleeding to find out the cause.

- have been diagnosed with a bleeding disorder
- currently have or have had certain cancers
  Estrogens may increase the chances of getting certain types of cancers, including cancer of the breast or uterus (womb). If you have or have had cancer, talk with your healthcare provider about whether you should use Divigel.
- had a stroke or heart attack
- currently have or have had blood clots
- currently have or have had liver problems
- are allergic to Divigel or any of its ingredients

See the list of ingredients in Divigel at the end of this leaflet.

Before you use Divigel, tell your healthcare provider about all of your medical conditions, including if you:

- have any unusual vaginal bleeding
  Vaginal bleeding after menopause may be a warning sign of cancer of the uterus (womb). Your healthcare provider should check any unusual vaginal bleeding to find out the cause.
- have any other medical conditions that may become worse while you are using Divigel
  Your healthcare provider may need to check you more carefully if you have certain conditions, such as asthma (wheezing), epilepsy (seizures), diabetes, migraines, endometriosis, lupus, angioedema (swelling of face and tongue), problems with your heart, liver, thyroid, kidneys, or have high calcium levels in your blood.
- are going to have surgery or will be on bedrest

Your healthcare provider will let you know if you need to stop using Divigel.

- are pregnant or think you may be pregnant
  Divigel is not for pregnant women.
- are breastfeeding
  The hormone in Divigel can pass into your breast milk.

Tell your healthcare provider about all the medicines you take, including prescription and over-the-counter medicines, vitamins, and herbal supplements. Some medicines may affect how Divigel works. Divigel may also affect how your other medicines work. Keep a list of your medicines and show it to your healthcare provider and pharmacist when you get new medicine.

How should I use Divigel?

- Take the dose recommended by your healthcare provider and talk to him or her about how well that dose is working for you.
- Estrogens should be used at the lowest dose possible for your treatment and only as long as needed.

You and your healthcare provider should talk regularly (for example, every 3 to 6 months) about the dose you are using and whether you still need treatment with Divigel.

How should Divigel be applied?

- Divigel should be applied 1-time a day, around the same time each day.
- Apply Divigel to clean, dry, and unbroken (without cuts or scrapes) skin. If you take a bath or shower, be sure to apply your Divigel after your skin is dry. The application site should be completely dry before dressing or swimming.
- Apply Divigel to either your left or right upper thigh. Change between your left and right upper thigh each day to help prevent skin irritation.

TO APPLY:

Step 1: Wash and dry your hands thoroughly.

Step 2: Sit in a comfortable position.

Step 3: Cut or tear the Divigel packet as shown in Figure A.

Figure A

Figure A

Step 4: Using your thumb and pointer (index) finger, squeeze the entire contents of the Divigel packet onto the skin of the upper thigh as shown in Figure B.

Figure B

Figure B

Step 5: Gently spread the gel in a thin layer on your upper thigh over an area of about 5 by 7 inches, or two palm prints as shown in Figure C. It is not necessary to massage or rub in Divigel.

Figure C

Figure C

Step 6: Allow the gel to dry completely before dressing.

Step 7: Throw away (dispose) of the empty Divigel packet in the trash.

Step 8: Wash your hands with soap and water immediately after applying Divigel to remove any remaining gel and reduce the chance of transferring Divigel to other people.

Important things to remember when using Divigel

- Allow the gel to dry before dressing. Try to keep the area dry for as long as possible.
- Do not allow another person to come in contact with the area of skin where you applied the gel for at least 1 hour after you apply Divigel.
- You should not have another person to apply the gel for you. However, if you need to have another person help you, have that person wear a disposable plastic glove to avoid direct contact with Divigel.
- Do not apply Divigel to your face, breast, or irritated skin.
- Never apply Divigel in or around the vagina.
- Divigel contains alcohol. Alcohol based gels are flammable. Avoid fire, flame or smoking until the gel has dried.

What should I do if I miss a dose?

If you miss a dose, do not double the dose on the next day to catch up. If your next dose is less than 12 hours away, it is best just to wait and apply your normal dose the next day. If it is more than 12 hours until the next dose, apply the dose you missed and resume your normal dosing the next day. Do not apply Divigel more than 1-time each day. If you accidentally spill some of the contents of a Divigel packet, do not open a new Divigel packet. Wait and apply your normal dose the next day.

What should I do if someone else is exposed to Divigel?

To reduce the chance of transfer to another person (or pet) let the Divigel dry completely. Wash your hands with soap and water after application. If someone else is exposed to Divigel by direct contact with the wet gel, have that person wash the area of contact with soap and water right away. This is especially important for men and children. The longer the gel is in contact with the skin before washing, the greater the chance that the other person (or pet) will absorb some of the estrogen hormone. This may harm them. In case of any signs or symptoms of estrogen exposure in the other person (or pet), contact your healthcare provider (or veterinarian, if appropriate).

What should I do if I get Divigel in my eyes?

If you get Divigel in your eyes, flush your eyes right away with lukewarm tap water. If you have concerns, contact your healthcare provider.

What are the possible side effects of Divigel?

Side effects are grouped by how serious they are and how often they happen when you are treated.

Serious, but less common side effects include:

- heart attack
- stroke
- blood clots
- breast cancer
- cancer of the lining of the uterus (womb)
- cancer of the ovary
- dementia
- high or low blood calcium (hypercalcemia)
- gall bladder disease
- visual abnormalities

- high blood pressure
- high levels of fat (triglycerides) in your blood
- liver problems
- changes in your thyroid hormone levels
- fluid retention
- cancer change of endometriosis
- enlargement of benign tumors of the uterus (“fibroids”)
- worsening swelling of face and tongue (angioedema)
- changes in certain laboratory test results such as high blood sugar

Call your healthcare provider right away if you get any of the following warning signs or any other unusual symptoms that concern you:

- new breast lumps
- unusual vaginal bleeding
- changes in vision or speech
- sudden new severe headaches
- severe pains in your chest or legs with or without shortness of breath, weakness, and fatigue
- swelling of face, lips, and tongue with or without red, itchy bumps

The most common side effects of Divigel include:

- irregular vaginal bleeding or spotting
- breast tenderness
- vaginal yeast infection
- upper respiratory tract (nose, sinuses, pharynx or larynx) infection

These are not all the possible side effects of Divigel. For more information, ask your healthcare provider or pharmacist for advice about side effects. Tell your healthcare provider if you have any side effects that bother you or do not go away. You may report side effects to FDA at 1-800-FDA-1088 or Vertical Pharmaceuticals, LLC at 1-800-444-5164.

What can I do to lower my chances of a serious side effect with Divigel?

- Talk with your healthcare provider regularly about whether you should continue using Divigel.
- If you have a uterus, talk to your healthcare provider about whether the addition of a progestogen is right for you.
- In general, the addition of a progestogen is recommended for a woman with a uterus to reduce the chance of getting cancer of the uterus (womb). See your healthcare provider right away if you get vaginal bleeding while using Divigel.
- Have a pelvic exam, breast exam and mammogram (breast X-ray) every year unless your healthcare provider tells you something else.
- If members of your family have had breast cancer or if you have ever had breast lumps or an abnormal mammogram, you may need to have breast exams more often.
- If you have high blood pressure, high cholesterol (fat in the blood), diabetes, are overweight, or if you use tobacco, you may have higher chances of getting heart disease.

Ask your healthcare provider for ways to lower your chances of getting heart disease.

How should I store Divigel?

Store Divigel packets at room temperature, 68 to 77ºF (20 to 25ºC).

Keep Divigel and all medicines out of the reach of children.

General information about safe and effective use of Divigel.

Medicines are sometimes prescribed for purposes other than those listed in a Patient Information leaflet. Do not use Divigel for a condition for which it was not prescribed. Do not give Divigel to other people, even if they have the same symptoms that you have. It may harm them.

This leaflet provides a summary of the most important information about Divigel. If you would like more information, talk with your healthcare provider or pharmacist. You can ask your healthcare provider or pharmacist for information about Divigel that is written for health professionals.

What are the ingredients in Divigel?

Active ingredient: estradiol.

Inactive ingredients: carbomer, ethanol, propylene glycol, purified water, and triethanolamine.

How is Divigel Supplied?

Divigel is supplied in individual foil packets, each one containing a single day's dose.

Manufactured by:
Orion Corporation Orion Pharma
Tengströminkatu 8
FI-20360 Turku
Finland

Distributed by:
VERTICAL PHARMACEUTICALS, LLC
Alpharetta, GA 30005 USA

1-800-444-5164

www.verticalpharma.com

Product of Finland

© 2023 Vertical Pharmaceuticals, LLC

151083-12
Revised 11/2023

This Patient Information has been approved by the U.S. Food and Drug Administration.

PRINCIPAL DISPLAY PANEL - .25 mg Packet Carton

NDC 68025-065-30

Divigel®
(estradiol gel) 0.1%

.25 mg

30 packets
.25 g gel provides .25 mg estradiol/packet

Rx only

VERTICAL
PHARMACEUTICALS, LLC

PRINCIPAL DISPLAY PANEL - .5 mg Packet Carton

NDC 68025-066-30

Divigel®
(estradiol gel) 0.1%

.5 mg

30 packets
.5 g gel provides .5 mg estradiol/packet

Rx only

VERTICAL
PHARMACEUTICALS, LLC

PRINCIPAL DISPLAY PANEL - .75 mg Packet Carton

NDC 68025-083-30

Divigel®
(estradiol gel) 0.1%

.75 mg

30 packets
.75 g gel provides .75 mg estradiol/packet

Rx only

VERTICAL
PHARMACEUTICALS, LLC

PRINCIPAL DISPLAY PANEL - 1 mg Packet Carton

NDC 68025-067-30

Divigel®
(estradiol gel) 0.1%

1 mg

30 packets
1 g gel provides 1 mg estradiol/packet

Rx only

VERTICAL
PHARMACEUTICALS, LLC

PRINCIPAL DISPLAY PANEL - 1.25 mg Packet Carton

NDC 68025-086-30

Divigel®
(estradiol gel) 0.1%

1.25 mg

30 packets
1.25 g gel provides 1.25 mg estradiol/packet

Rx only

VERTICAL
PHARMACEUTICALS, LLC